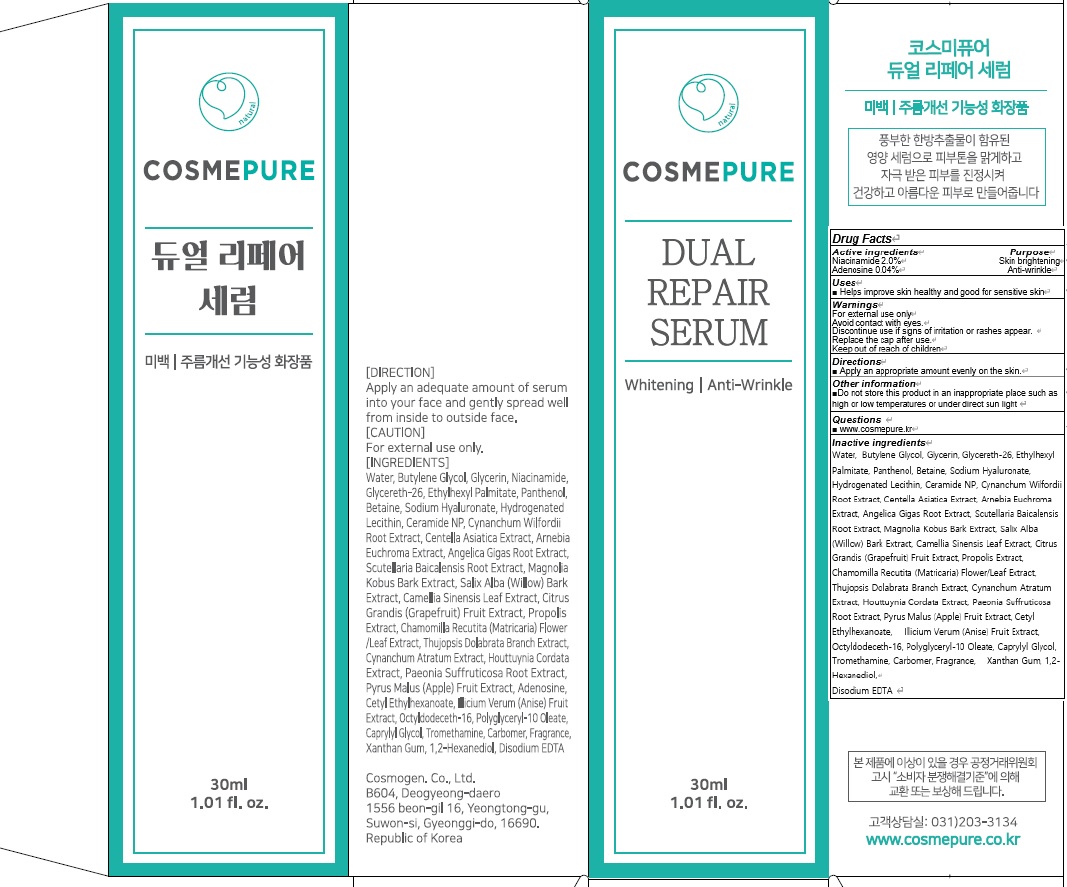 DRUG LABEL: COSMEPURE DUAL REPAIR SERUM
NDC: 81418-050 | Form: LIQUID
Manufacturer: Cosmogen Co., Ltd.
Category: otc | Type: HUMAN OTC DRUG LABEL
Date: 20210129

ACTIVE INGREDIENTS: Niacinamide 0.6 g/30 mL; Adenosine 0.012 g/30 mL
INACTIVE INGREDIENTS: Water; Butylene Glycol

ACTIVE INGREDIENTS

Niacinamide 2.0%
Adenosine 0.04%

INACTIVE INGREDIENTS

Water, Butylene Glycol, Glycerin, Glycereth-26, Ethylhexyl Palmitate, Panthenol, Betaine, Sodium Hyaluronate, Hydrogenated Lecithin, Ceramide NP, Cynanchum Wilfordii Root Extract, Centella Asiatica Extract, Arnebia Euchroma Extract, Angelica Gigas Root Extract, Scutellaria Baicalensis Root Extract, Magnolia Kobus Bark Extract, Salix Alba (Willow) Bark Extract, Camellia Sinensis Leaf Extract, Citrus Grandis (Grapefruit) Fruit Extract, Propolis Extract, Chamomilla Recutita (Matricaria) Flower/Leaf Extract, Thujopsis Dolabrata Branch Extract, Cynanchum Atratum Extract, Houttuynia Cordata Extract, Paeonia Suffruticosa Root Extract, Pyrus Malus (Apple) Fruit Extract, Cetyl Ethylhexanoate, Illicium Verum (Anise) Fruit Extract, Octyldodeceth-16, Polyglyceryl-10 Oleate, Caprylyl Glycol, Tromethamine, Carbomer, Fragrance, Xanthan Gum, 1,2-Hexanediol,
Disodium EDTA

PURPOSE

Skin brightening
Anti wrinkle

WARNINGS

For external use only
Avoid contact with eyes.
Discontinue use if signs of irritation or rashes appear.
Replace the cap after use.
Keep out of reach of children

KEEP OUT OF REACH OF CHILDREN

Uses

■ Helps improve skin healthy and good for sensitive skin

Directions

■ Apply an appropriate amount evenly on the skin.

Other information

■ Do not store this product in an inappropriate place such as high or low temperatures or under direct sun light

QUESTIONS

■ www.cosmepure.kr